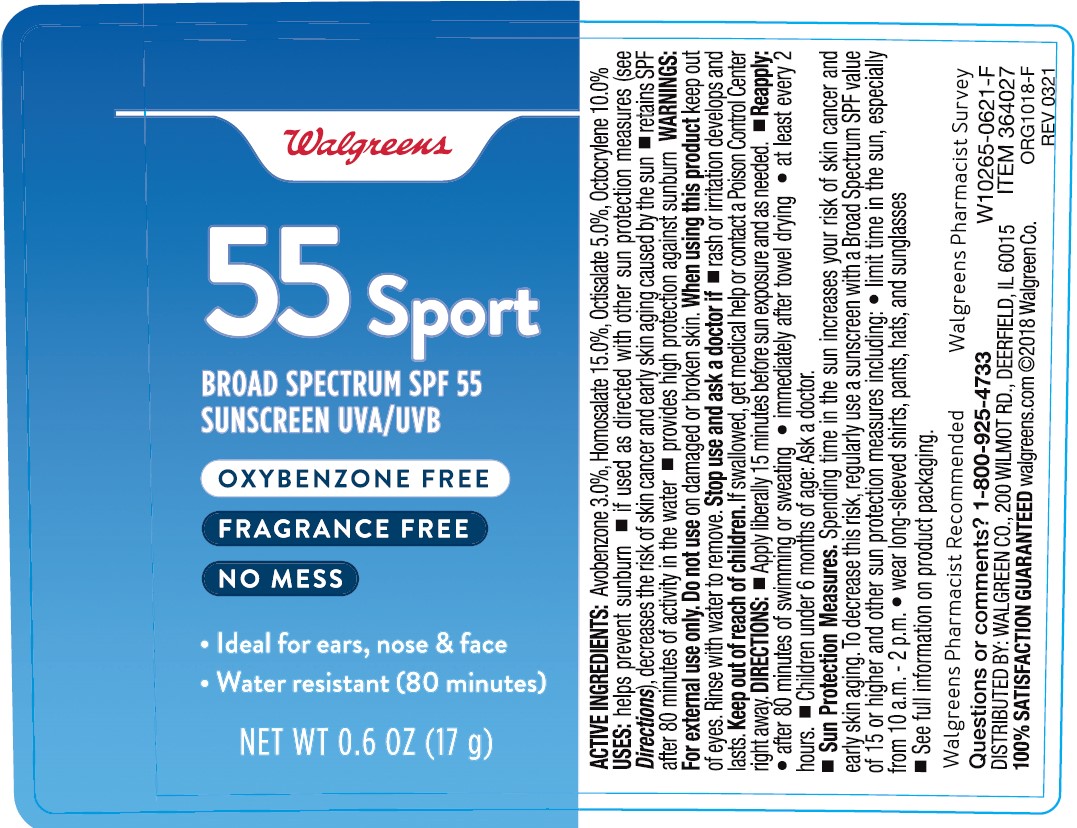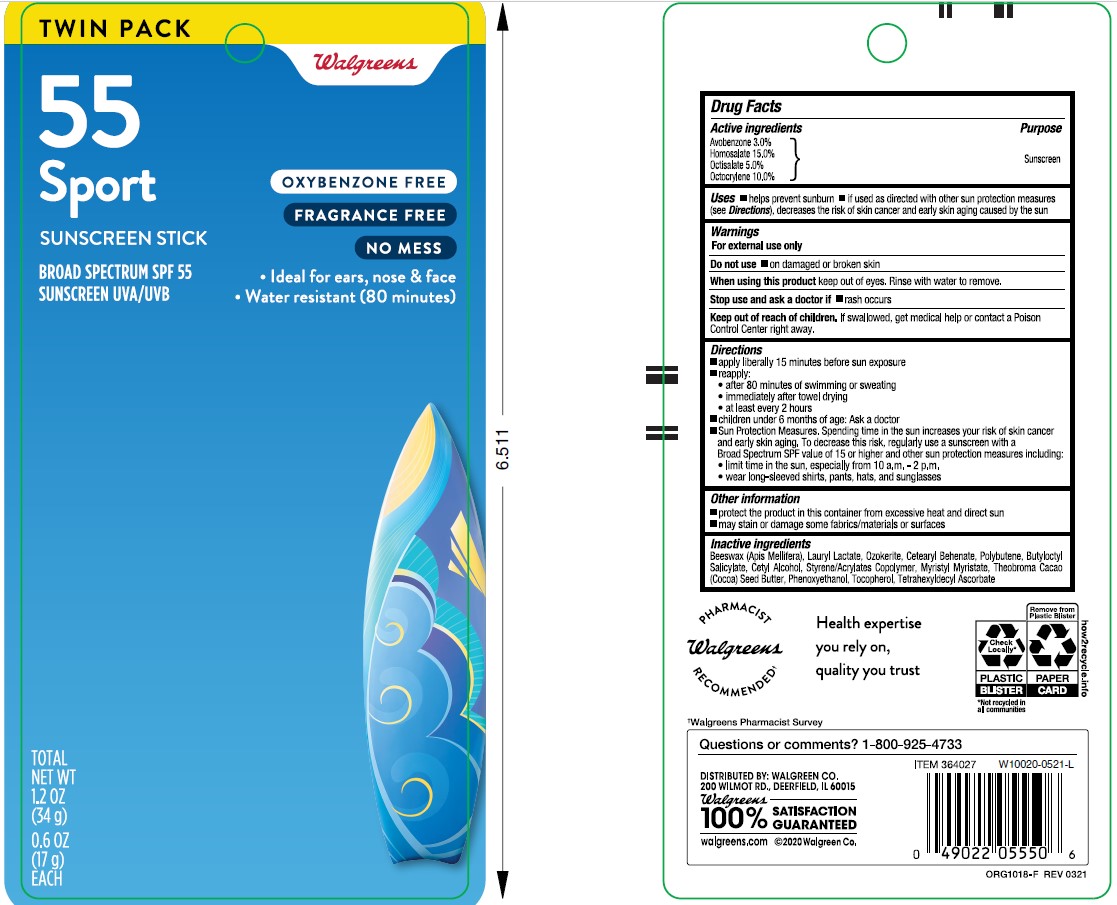 DRUG LABEL: Walgreens SPF55 Sunscreen Reef-Conscious Formula
NDC: 0363-0976 | Form: STICK
Manufacturer: WALGREEN COMPANY
Category: otc | Type: HUMAN OTC DRUG LABEL
Date: 20241014

ACTIVE INGREDIENTS: OCTISALATE 50 mg/1 g; HOMOSALATE 150 mg/1 g; OCTOCRYLENE 100 mg/1 g; AVOBENZONE 30 mg/1 g
INACTIVE INGREDIENTS: POLYBUTENE (1400 MW); ASCORBYL TETRAISOPALMITATE; STYRENE/ACRYLAMIDE COPOLYMER (MW 500000); .ALPHA.-TOCOPHEROL, DL-; PHENOXYETHANOL; THEOBROMA CACAO WHOLE; LAURYL LAURATE; CERESIN; BUTYLOCTYL SALICYLATE; WHITE WAX; CETEARYL BEHENATE; MYRISTYL MYRISTATE

Walgreens SPF55 Sunscreen Stick Reef-Conscious Formula

Active ingredients

Avobenzone 3.0%

Homosalate 15.0%

Octisalate 5.0%

Octocrylene 10.0%

Purpose

Sunscreen

Uses

• helps prevent sunburn • if used as directed with other sun protection measures (see Directions), decreases the risk of skin cancer and early skin aging caused by the sun

Warnings

For external use only

Do not use

•on damaged or broken skin.

When using this product

• keep out of eyes. Rinse with water to remove.

Stop use and ask a doctor if

• rash occurs.

Keep out of reach of children

If product is swallowed, get medical help or contact a Poison Control Poison Control Center right away.

Directions

• apply liberally 15 minutes before sun exposure

• reapply:

• after 80 minutes of swimming or sweating

• immediately after towel drying

• at least every 2 hours

• children under 6 months of age: Ask a doctor

• Sun Protection Measures. Spending time in the sun increases your risk of skin cancer and early skin aging. To decrease this risk, regularly use a sunscreen with a broad spectrum SPF of 15 or higher and other sun protection measures including:

• limit time in the sun, especially from 10 a.m. - 2 p.m.

• wear long-sleeve shirts, pants, hats, and sunglasses

Other information

• protect the product in this container from excessive heat and direct sun

• may stain or damage some fabrics, materials, or surfaces

Inactive ingredients

beeswax (apis mellifera), lauryl laurate, ozokerite, cetearyl behenate, polybutene, butyloctyl salicylate, cetyl alcohol, styrene acrylates copolymer, myristyl myristate, theobroma cacao (cocoa) seed butter, phenoxyethanol, tocopherol, tetrahexyldecyl ascorbate